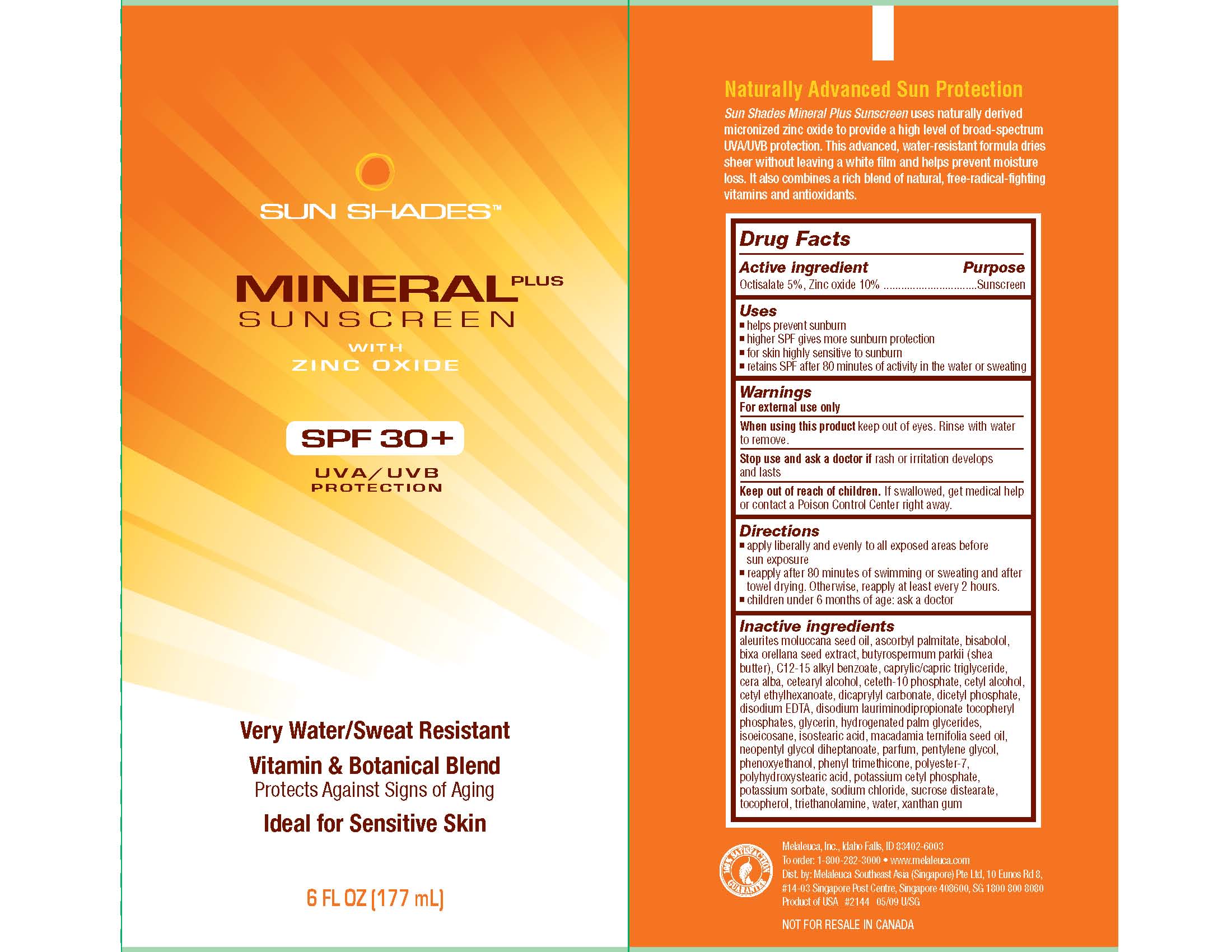 DRUG LABEL: Sun Shades
NDC: 54473-164 | Form: CREAM
Manufacturer: Melaleuca, Inc.
Category: otc | Type: HUMAN OTC DRUG LABEL
Date: 20110223

ACTIVE INGREDIENTS: OCTISALATE 9.225 g/177 mL; ZINC OXIDE 18.45 g/177 mL
INACTIVE INGREDIENTS: ALPHA-TOCOPHEROL ACETATE; ASCORBYL PALMITATE; BIXA ORELLANA SEED; C12-15 ALKYL BENZOATE; CETOSTEARYL ALCOHOL; CETYL ALCOHOL; CETYL ETHYLHEXANOATE; DICAPRYLYL CARBONATE; DIHEXADECYL PHOSPHATE; EDETATE DISODIUM; GLYCERIN; ISOSTEARIC ACID; KUKUI NUT OIL; LEVOMENOL; MACADAMIA OIL; MEDIUM-CHAIN TRIGLYCERIDES; NEOPENTYL GLYCOL DIHEPTANOATE; PENTYLENE GLYCOL; PHENOXYETHANOL; PHENYL TRIMETHICONE; POLYHYDROXYSTEARIC ACID (2300 MW); POTASSIUM CETYL PHOSPHATE; POTASSIUM SORBATE; SHEA BUTTER; SODIUM CHLORIDE; TROLAMINE; WATER; XANTHAN GUM; YELLOW WAX

Sun Shades Mineral SPF 30+ Content of Label

Active ingredient
Octisalate 5%, Zinc oxide 10%

Purpose
Sunscreen

Uses

- helps prevent sunburn
- higher SPF gives more sunburn protection
- for skin highly sensitive to sunburn
- retains SPF after 80 minutes of activity in the water or sweating

Warnings
For external use only

When using this product keep out of the eyes. Rinse with water to remove.

Stop use and ask a doctor if rash or irritation develops and lasts

Keep out of reach of children. If swallowed, get medical help or contact a Poison Control Center right away.

Directions

- apply liberally and evenly to all exposed areas before sun exposure
- reapply after 80 minutes of swimming or sweating and after towel drying. Otherwise, reapply at least every 2 hours.
- children under 6 months of age: ask a doctor

Inactive ingredients
aleurites moluccana seed oil, ascorbyl palmitate, bisabolol, bixa orellana seed extract, butyrospermum parkii (shea butter), C12-15 alkyl benzoate, caprylic/capric triglyceride, cera alba, cetearyl alcohol, ceteth-10 phosphate, cetyl alcohol, cetyl ethylhexanoate, dicaprylyl carbonate, dicetyl phosphate, disodium EDTA, disodium lauriminodipropionate tocopheryl phosphates, glycerin, hydrogenated palm glycerides, isoeicosane, isostearic acid, macadamia ternifolia seed oil, neopentyl glycol diheptanoate, parfum, pentylene glycol, phenoxyethanol, phenyl trimethicone, polyester-7, polyhydroxystearic acid, potassium cetyl phosphate, potassium sorbate, sodium chloride, sucrose distearate, tocopherol, triethanolamine, water, xanthan gum